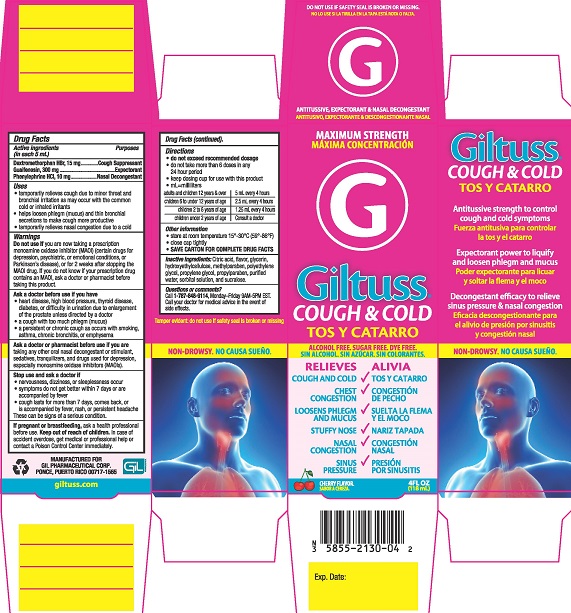 DRUG LABEL: Giltuss Cough and Cold
NDC: 58552-130 | Form: SOLUTION
Manufacturer: Gil Pharmaceutical Corp
Category: otc | Type: HUMAN OTC DRUG LABEL
Date: 20251009

ACTIVE INGREDIENTS: DEXTROMETHORPHAN HYDROBROMIDE 15 mg/5 mL; GUAIFENESIN 300 mg/5 mL; PHENYLEPHRINE HYDROCHLORIDE 10 mg/5 mL
INACTIVE INGREDIENTS: WATER; POLYETHYLENE GLYCOL, UNSPECIFIED; SORBITOL; SUCRALOSE; ANHYDROUS CITRIC ACID; PROPYLPARABEN; PROPYLENE GLYCOL; METHYLPARABEN; HYDROXYETHYL CELLULOSE (2000 MPA.S AT 1%); GLYCERIN

Giltuss Cough & Cold

Drug Facts

Active ingredients (in each 5 mL)

Dextromethorphan HBr, 15 mg

Guaifenesin, 300 mg

Phenylephrine HCI, 10 mg

Purposes

Cough Suppressant

Expectorant

Nasal Decongestant

Uses

- temporarily relieves cough due to minor throat and bronchial irritation as may occur with the common cold or inhaled irritants
- helps loosen phlegm (mucus) and thin bronchial secretions to make cough more productive
- temporarily relieves nasal congestion due to a cold

Warnings

DO NOT USE

Do not useif you are taking a prescription monoamine oxidase inhibitor (MAOI) (certain drugs for depression, psychiatric, or emotional conditions, or Parkinson's disease), or for 2 weeks after stopping the MAOI drug. If you do not know if your prescription drug contains an MAOI, ask a doctor or pharmacist before taking this product.

Ask a doctor before use if you have

- heart disease, high blood pressure, thyroid disease, or diabetes, or difficulty in urination due to enlargement of the prostate gland unless directed by a doctor
- a cough with too much phlegm (mucus)
- a persistent or chronic cough such as occurs with smoking, chronic bronchitis, or emphysema

Ask a doctor or pharmacist before use if you aretaking any other oral nasal decongestant or stimulant, sedatives, tranquilizers, and drugs for depression, especially monoamine oxidase inhibitors (MAOIs).

Stop use and ask a doctor if

- nervousness, dizziness, or sleeplessness occur
- symptoms do not get better within 7 days or are accompanied by fever
- cough lasts for more than 7 days, comes back, or occurs with fever, rash or persistant headache

These can be signs of a serious condition.

PREGNANCY OR BREAST FEEDING

If pregnant or breast-feeding,ask a health professional before use.

Keep out of reach of children.In case of accident overdose, get medical or professional help or contact a Poison Control Center immediately.

Directions

- do not exceed recommended dosage
- do not take more than 6 doses in any 24 hour period
- keep dosing cup for use with this product
- mL = milliliters

adults and children 12 years & over | 5 mL every 4 hours
children 6 to under 12 years of age | 2.5 mL every 4 hours
children 2 to 6 years of age | 1.25 mL every 4 hours
children under 2 years of age | Consult a doctor

Other information

- store at room temperature 15°- 30°C (59° - 86°F)
- close cap tightlly
- SAVE CARTON FOR COMPLETE DRUG FACTS

INACTIVE INGREDIENT

Inactive ingredientsCitric acid, flavor, glycerin, hydroxyethylcellulose, methylparaben, polyethylene glycol, propylene glycol, propylparaben, purified water, sorbitol solution, and sucralose.

Questions or comments?

Call 1-787-848-9114, Monday - Friday 9AM - 5PM EST. Call your doctor for medical advice in the event of side effects.

Tamper evident: do not use if safety seal is broken or missing

MANUFACTURED FOR

GIL PHARMACEUTICAL CORP.

PONCE, PUERTO RICO 00717-1565

PACKAGE LABEL

MAXIMUM STRENGTH

GILTUSS®

COUGH & COLD

ALCOHOL FREE. SUGAR FREE. DYE FREE

RELIEVES

- COUGH AND COLD
- CHEST CONGESTION
- LOOSENS PHLEGM AND MUCUS
- STUFFY NOSE
- NASAL CONGESTION
- SINUS PRESSURE

4 FL OZ (118 mL)